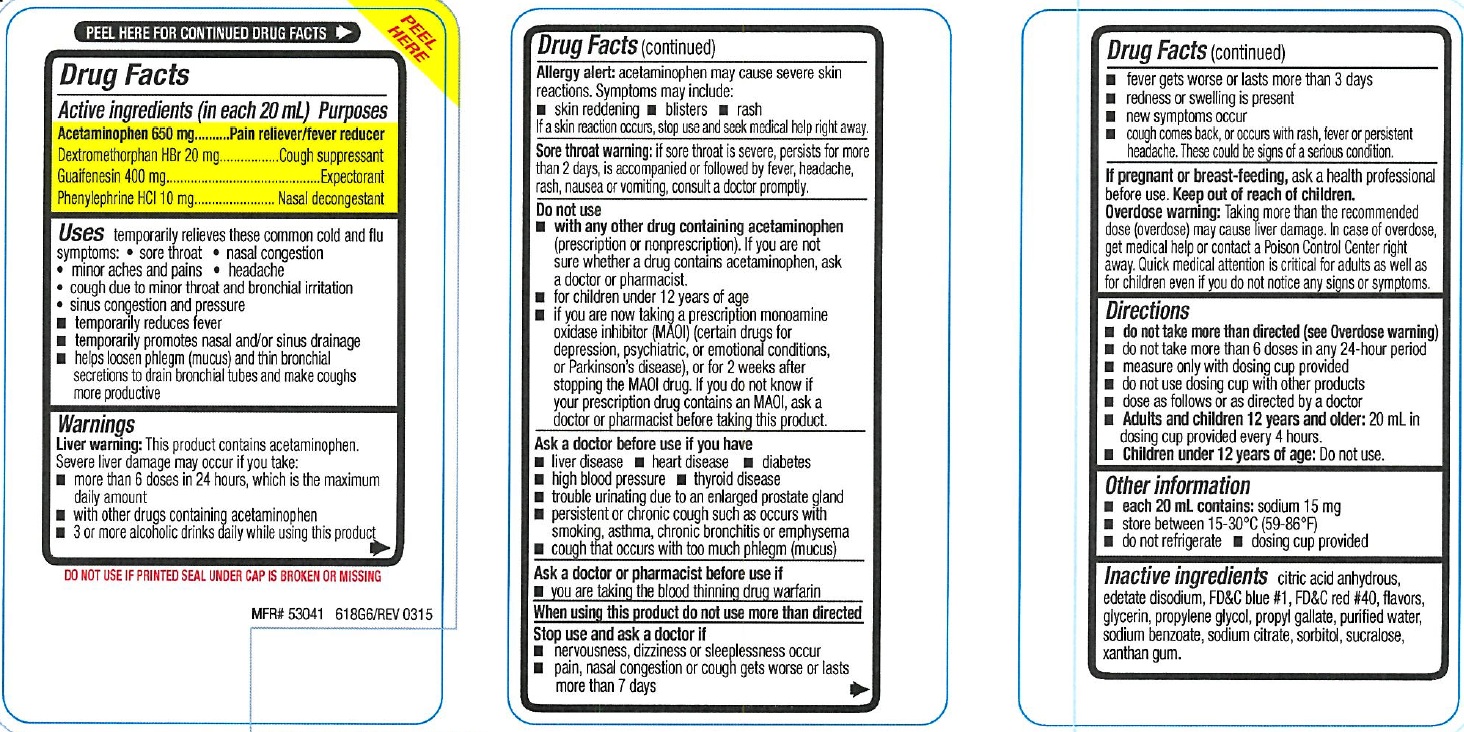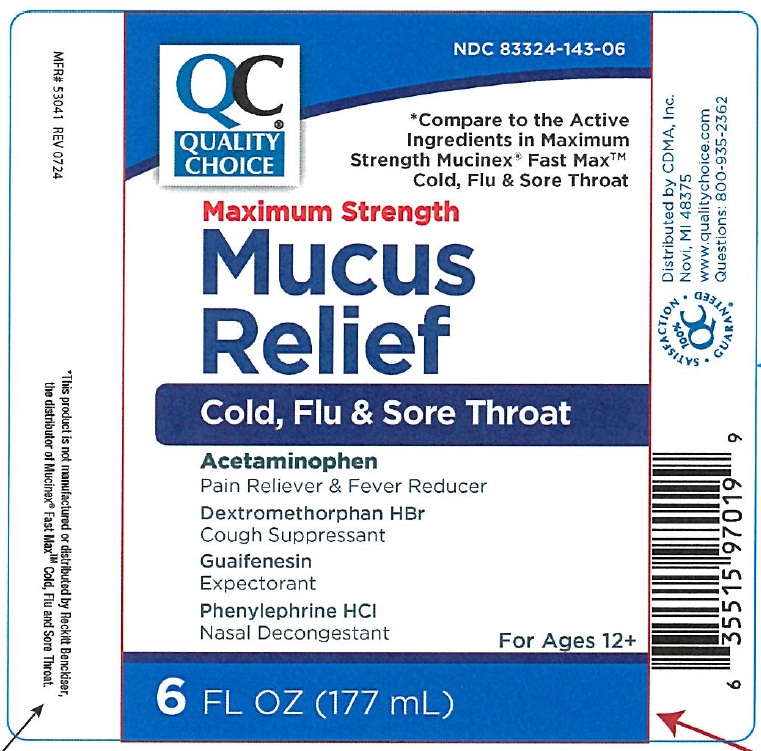 DRUG LABEL: Maximum Strength Mucus Relief
NDC: 83324-143 | Form: LIQUID
Manufacturer: Chain Drug Marketing Association Inc.
Category: otc | Type: Human OTC Drug Label
Date: 20250213

ACTIVE INGREDIENTS: DEXTROMETHORPHAN HYDROBROMIDE 20 mg/20 mL; GUAIFENESIN 400 mg/20 mL; PHENYLEPHRINE HYDROCHLORIDE 10 mg/20 mL; ACETAMINOPHEN 650 mg/20 mL
INACTIVE INGREDIENTS: ANHYDROUS CITRIC ACID; EDETATE DISODIUM; FD&C BLUE NO. 1; FD&C RED NO. 40; GLYCERIN; PROPYLENE GLYCOL; PROPYL GALLATE; WATER; SODIUM BENZOATE; SODIUM CITRATE, UNSPECIFIED FORM; SORBITOL; SUCRALOSE; XANTHAN GUM

Maximum Strength Mucus Relief

ACTIVE INGREDIENTS (in each 20 mL)

Acetaminophen 650 mg

Dextromethorphan HBr 20 mg
Guaifenesin 400 mg
Phenylephrine HCI 10 mg

PURPOSE

Pain reliever/fever reducer

Cough suppressant

Expectorant

Nasal decongestant

USE(S)

temporarily relieves these common cold and flu symptoms:

- sore throat
- nasal congestion
- minor aches and pains
- headache
- cough due to minor throat and bronchial irritation
- sinus congestion and pressure

- temporarily reduces fever
- temporarily promotes nasal and/or sinus drainage
- helps loosen phlegm (mucus) and thin bronchial secretions to drain bronchial tubes and make coughs more productive

WARNINGS

Liver warning: This product contains acetaminophen.
Severe liver damage may occur if you take:

- more than 6 doses in 24 hours, which is the maximum
  daily amount
- with other drugs containing acetaminophen
- 3 or more alcoholic drinks daily while using this product

Allergy alert: acetaminophen may cause severe skin
reactions. Symptoms may include:

- skin reddening
- blisters
- rash

If a skin reaction occurs, stop use and seek medical help right away.

Sore throat warning: if sore throat is severe, persists for more than 2 days, is accompanied or followed by fever, headache, rash, nausea or vomiting, consult a doctor promptly.

DO NOT USE

- with any other drug containing acetaminophen (prescription or nonprescription). If you are not sure whether a drug contains acetaminophen, ask a doctor or pharmacist.
- for children under 12 years of age
- if you are now taking a prescription monoamine oxidase inhibitor (MAOI) (certain drugs for depression, psychiatric, or emotional conditions,
  or Parkinson’s disease), or for 2 weeks after stopping the MAOI drug. If you do not know if your prescription drug contains an MAOI, ask a
  doctor or pharmacist before taking this product.

ASK A DOCTOR BEFORE USE IF YOU HAVE

• liver disease

• heart disease

• diabetes
• high blood pressure
• thyroid disease
• trouble urinating due to an enlarged prostate gland
• persistent or chronic cough such as occurs with smoking, asthma, chronic bronchitis or emphysema
• cough that occurs with too much phlegm (mucus)

ASK A DOCTOR OR PHARMACIST BEFORE USE IF

you are taking the blood thinning drug warfarin

WHEN USING THIS PRODUCT

• do not use more than directed

STOP USE AND ASK DOCTOR IF

- nervousness, dizziness or sleeplessness occur
- pain, nasal congestion or cough gets worse or lasts more than 7 days
- fever gets worse or lasts more than 3 days
- redness or swelling is present
- new symptoms occur
- cough comes back, or occurs with rash, fever or persistent headache. These could be signs of a serious condition.

IF PREGNANT OR BREAST FEEDING

ask a health professional before use.

KEEP OUT OF REACH OF CHILDREN

Overdose warning: Taking more than the recommended dose (overdose) may cause liver damage. In case of overdose, get medical help or contact a Poison Control Center right away. Quick medical attention is critical for adults as well as for children even if you do not notice any signs or symptoms.

DIRECTIONS

- do not take more than directed (see Overdose warning)
- do not take more than 6 doses in any 24-hour period
- measure only with dosing cup provided
- do not use dosing cup with other products
- dose as follows or as directed by a doctor
- Adults and children 12 years and older: 20 mL in dosing cup provided every 4 hours.
- Children under 12 years of age: Do not use.

OTHER INFORMATION

• each 20 ml contains: sodium 15 mg
• store between 15-30ºC (59-86ºF)
• do not refrigerate
• dosing cup provided

INACTIVE INGREDIENTS

citric acid anhydrous, edetate disodium, FD&C blue #1, FD&C red #40, flavors, glycerin, propylene glycol, propyl gallate, purified water, sodium benzoate, sodium citrate, sorbitol, sucralose, xanthan gum.

PRINCIPAL DISPLAY PANEL

NDC 83324-143-06

QC® QUALITY CHOICE

*Compare to the Active Ingredients in Maximum Strength Mucinex® Fax Max™ Cold, Flu & Sore Throat

Maximum Strength Mucus Relief

Cold, Flu & Sore Throat

Acetaminophen

Pain Reliever & Fever Reducer

Dextromethorphan HBr

Cough Suppressant
Guaifenesin

Expectorant
Phenylephrine HCI

Nasal Decongestant

For Ages 12+

6 FL OZ (177 mL)